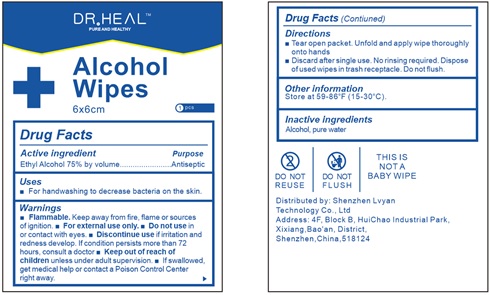 DRUG LABEL: Dr.Heal Alcohol Pads
NDC: 78031-301 | Form: CLOTH
Manufacturer: Shenzhen Lvyan Technology Co., Ltd.
Category: otc | Type: HUMAN OTC DRUG LABEL
Date: 20200603

ACTIVE INGREDIENTS: ALCOHOL 0.7 g/1 1
INACTIVE INGREDIENTS: WATER

Dr.Heal Alcohol Pads

Dr.Heal Alcohol Pads

Active Ingredient(s)

ALCOHOL 0.7g/pcs. Purpose: Antiseptic

Purpose

Antiseptic, Dr.Heal Alcohol Pads

Use

Dr.Heal Alcohol Pads to help reduce bacteria that potentially can cause disease. For use when soap and water are not available.

Warnings

For external use only. Flammable. Keep away from heat or flame

Do not use

- in children less than 2 months of age
- on open skin wounds

When using this product keep out of eyes, ears, and mouth. In case of contact with eyes, rinse eyes thoroughly with water.
Stop use and ask a doctor if irritation or rash occurs. These may be signs of a serious condition.
Keep out of reach of children. If swallowed, get medical help or contact a Poison Control Center right away.

Stop use and ask a doctor if irritation or rash occurs. These may be signs of a serious condition.

Keep out of reach of children. If swallowed, get medical help or contact a Poison Control Center right away.

Directions

- Tear open packet. Unfold and apply wipe thoroughly onto hands or surfaces.
- Discard after single use. No rinsing required.
- Dispose of used wipes in trash receptacle. Do not flsuh.
- Supervise children under 6 years of age when using this product to avoid swallowing.

Other information

- Store between 15-30C (59-86F)
- Avoid freezing and excessive heat above 40C (104F)

Inactive ingredients

purified water USP